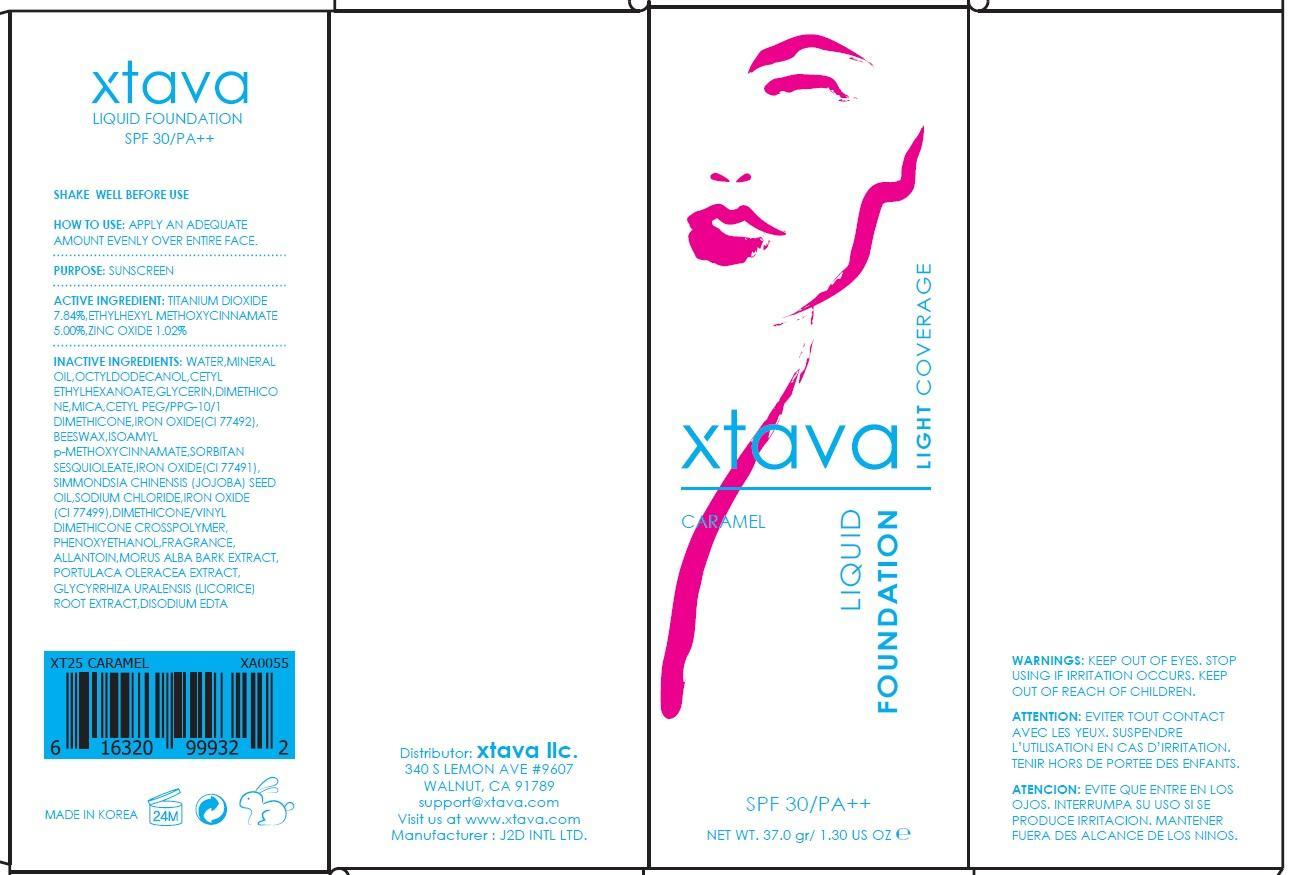 DRUG LABEL: FOUNDATION CARAMEL
NDC: 69958-030 | Form: LIQUID
Manufacturer: J2D INTERNATIONAL
Category: otc | Type: HUMAN OTC DRUG LABEL
Date: 20150716

ACTIVE INGREDIENTS: TITANIUM DIOXIDE 2.90 g/37 g; OCTINOXATE 1.85 g/37 g; ZINC OXIDE 0.37 g/37 g
INACTIVE INGREDIENTS: WATER; MINERAL OIL

ACTIVE INGREDIENT

Active Ingredient: TITANIUM DIOXIDE 7.84%, ETHYLHEXYL METHOXYCINNAMATE 5.00%, ZINC OXIDE 1.02%

INACTIVE INGREDIENT

Inactive Ingredients: WATER, MINERAL OIL, OCTYLDODECANOL, CETYL ETHYLHEXANOATE, GLYCERIN, DIMETHICONE, MICA, CETYL PEG/PPG-10/1 DIMETHICONE, IRON OXIDE(Cl 77492), BEESWAX, ISOAMYL p-METHOXYCINNAMATE, SORBITAN SESQUIOLEATE, IRON OXIDE(Cl 77491), SIMMONDSIA CHINENSIS (JOJOBA) SEED OIL, SODIUM CHLORIDE, IRON OXIDE(Cl 77499), DIMETHICONE/VINYL DIMETHICONE CROSSPOLYMER, PHENOXYETHANOL, PERFUME, ALLANTOIN, MORUS ALBA BARK EXTRACT, PORTULACA OLERACEA EXTRACT, GLYCYRRHIZA URALENSIS (LICORICE) ROOT EXTRACT, DISODIUM EDTA

PURPOSE

Purpose: Sunscreen

WARNINGS

Warnings: KEEP OUT OF EYES. STOP USING IF IRRITATION OCCURS. KEEP OUT OF REACH OF CHILDREN.

DESCRIPTION

ATTENTION: EVITER TOUT CONTACT AVEC LES YEUX. SUSPENDRE L’UTILISATION EN CAS D’IRRITATION. TENIR HORS DE PORTEE DES ENFANTS.

ATENCION: EVITE QUE ENTRE EN LOS OJOS. INTERRUMPA SU USO SI SE PRODUCE IRRITACION. MANTENER FUERA DES ALCANCE DE LOS NINOS.

How to use: APPLY AN ADEQUATE AMOUNT EVENLY OVER ENTIRE FACE.